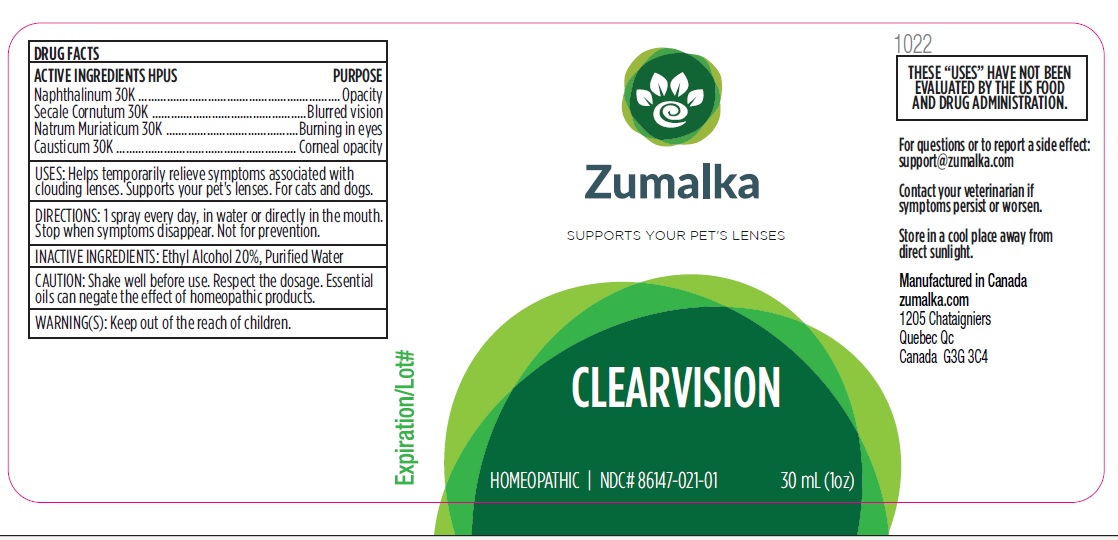 DRUG LABEL: CLEARVISION
NDC: 86147-021 | Form: LIQUID
Manufacturer: Groupe Cyrenne Inc.
Category: homeopathic | Type: OTC ANIMAL DRUG LABEL
Date: 20251120

ACTIVE INGREDIENTS: NAPHTHALENE 30 [kp_C]/30 mL; CLAVICEPS PURPUREA SCLEROTIUM 30 [kp_C]/30 mL; SODIUM CHLORIDE 30 [kp_C]/30 mL; CAUSTICUM 30 [kp_C]/30 mL
INACTIVE INGREDIENTS: WATER; ALCOHOL

Active ingredient Purpose

Naphthalinum 30k Opacity

Secale Cornutum 30k Blurred vision

Natrum Muriaticum 30k Burning in eyes

Causticum 30k Corneal opacity

Uses

Helps temporarily relieve symptoms associated with clouding lenses. Supports your pet's lens. For cats and dogs.

Warnings

Keep out of reach of children.

Direction

1 spray every day, in water or directly in the mouth. Stop when symptoms disappear. Not for prevention.

Inactive ingredient

Ethyl alcohol 20%, purified water

Cautions

Shake well before use. Respect the dosage. Essential oils can negate the effects of homeopathic products. Store in a cool place away from direct sunlight.